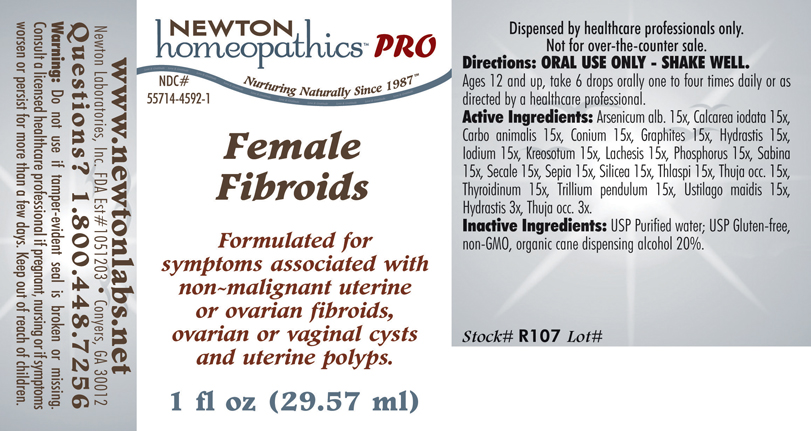 DRUG LABEL: Female Fibroids 
NDC: 55714-4592 | Form: LIQUID
Manufacturer: Newton Laboratories, Inc.
Category: homeopathic | Type: HUMAN PRESCRIPTION DRUG LABEL
Date: 20110601

ACTIVE INGREDIENTS: Arsenic Trioxide 15 [hp_X]/1 mL; Calcium Iodide 15 [hp_X]/1 mL; Carbo Animalis 15 [hp_X]/1 mL; Conium Maculatum Flowering Top 15 [hp_X]/1 mL; Graphite 15 [hp_X]/1 mL; Goldenseal 15 [hp_X]/1 mL; Iodine 15 [hp_X]/1 mL; Wood Creosote 15 [hp_X]/1 mL; Lachesis Muta Venom 15 [hp_X]/1 mL; Phosphorus 15 [hp_X]/1 mL; Juniperus Sabina Leafy Twig 15 [hp_X]/1 mL; Claviceps Purpurea Sclerotium 15 [hp_X]/1 mL; Sepia Officinalis Juice 15 [hp_X]/1 mL; Silicon Dioxide 15 [hp_X]/1 mL; Capsella Bursa-pastoris 15 [hp_X]/1 mL; Thuja Occidentalis Leafy Twig 15 [hp_X]/1 mL; Thyroid, Unspecified 15 [hp_X]/1 mL; Trillium Erectum Root 15 [hp_X]/1 mL; Ustilago Maydis 15 [hp_X]/1 mL
INACTIVE INGREDIENTS: Alcohol

Female Fibroids

INDICATIONS & USAGE SECTION

FEMALE FIBROIDS Formulated for symptoms associated with non-malignant uterine or ovarian fibroids, ovarian or vaginal cysts and uterine polyps.

DOSAGE & ADMINISTRATION SECTION

Directions: ORAL USE ONLY - SHAKE WELL. Ages 12 and up, take 6 drops orally one to four times daily or as directed by a healthcare professional.

ACTIVE INGREDIENT SECTION

Arsenicum alb. 15x, Calcarea iodata 15x, Carbo animalis 15x, Conium 15x, Graphites 15x, Hydrastis 15x, Iodium 15x, Kreosotum 15x, Lachesis 15x, Phosphorus 15x, Sabina 15x, Secale 15x, Sepia 15x, Silicea 15x, Thlaspi 15x, Thuja occ. 15x, Thyroidinum 15x, Trillium pendulum 15x, Ustilago maidis 15x, Hydrastis 3x, Thuja occ. 3x.

PURPOSE SECTION

Formulated for symptoms associated with non-malignant uterine or ovarian fibroids, ovarian or vaginal cysts and uterine polyps.

INACTIVE INGREDIENT SECTION

Inactive Ingredients: USP Purified Water; USP Gluten-free, non-GMO, organic cane dispensing alcohol 20%.

QUESTIONS? SECTION

www.newtonlabs.net Newton Laboratories, Inc. FDA Est # 1051203 - Conyers, GA 30012
Questions? 1.800.448.7256

WARNINGS SECTION

Warning: Do not use if tamper - evident seal is broken or missing. Consult a licensed healthcare professional if pregnant, nursing or if symptoms worsen or persist for more than a few days. Keep out of reach of children.

PREGNANCY OR BREAST FEEDING SECTION

Consult a licensed healthcare professional if pregnant or nursing or if symptoms worsen or persist for more than a few days.

KEEP OUT OF REACH OF CHILDREN SECTION

Keep out of reach of children.